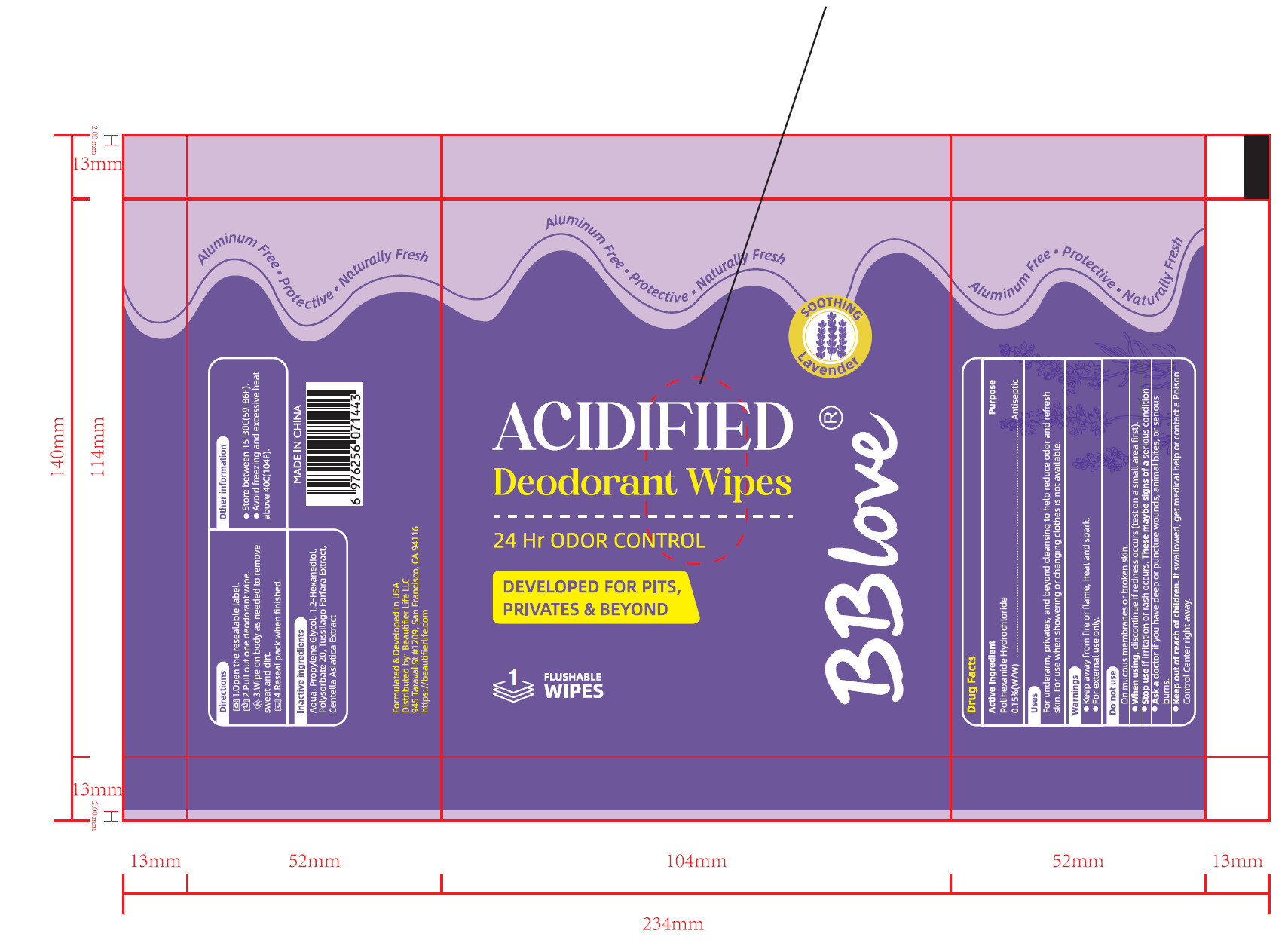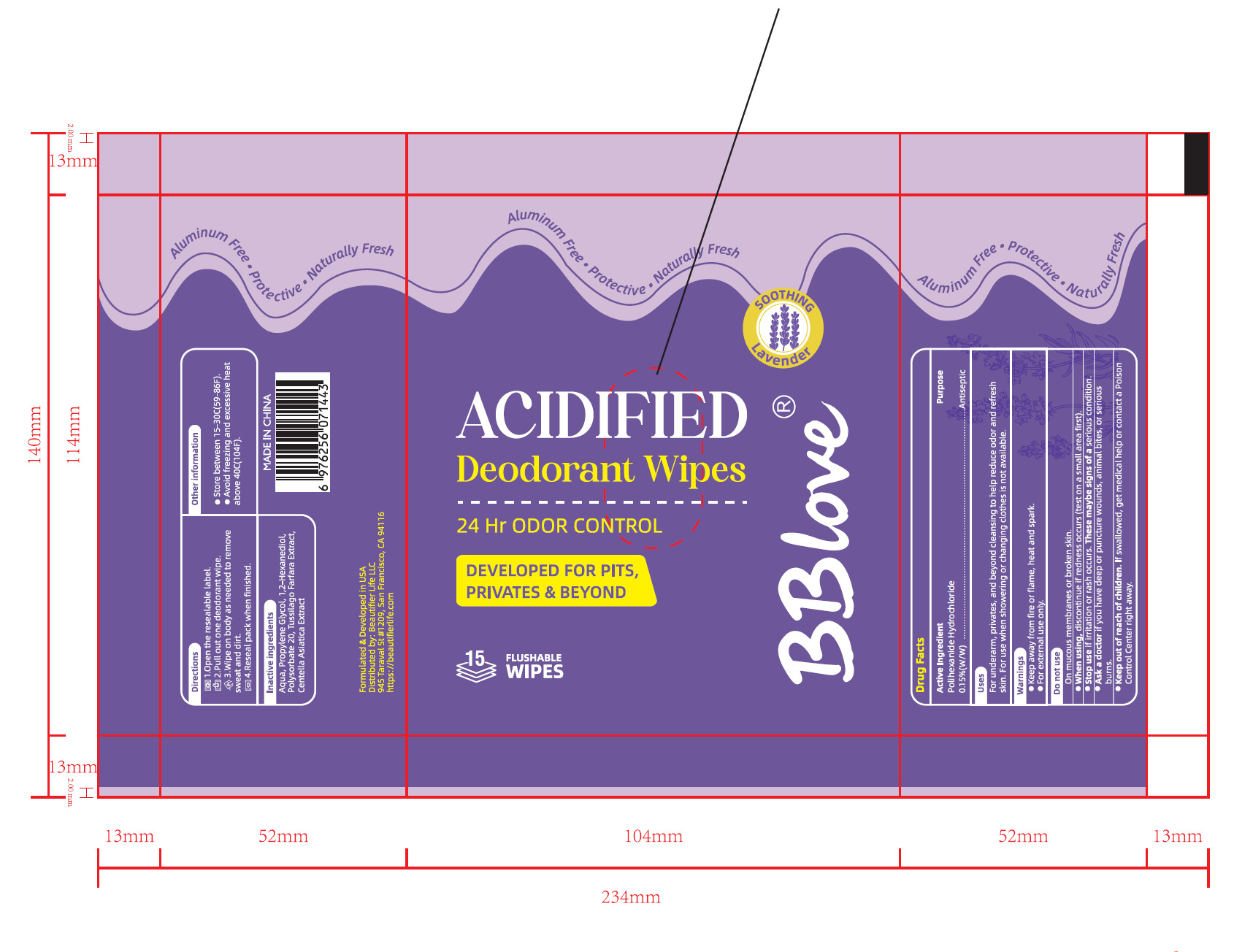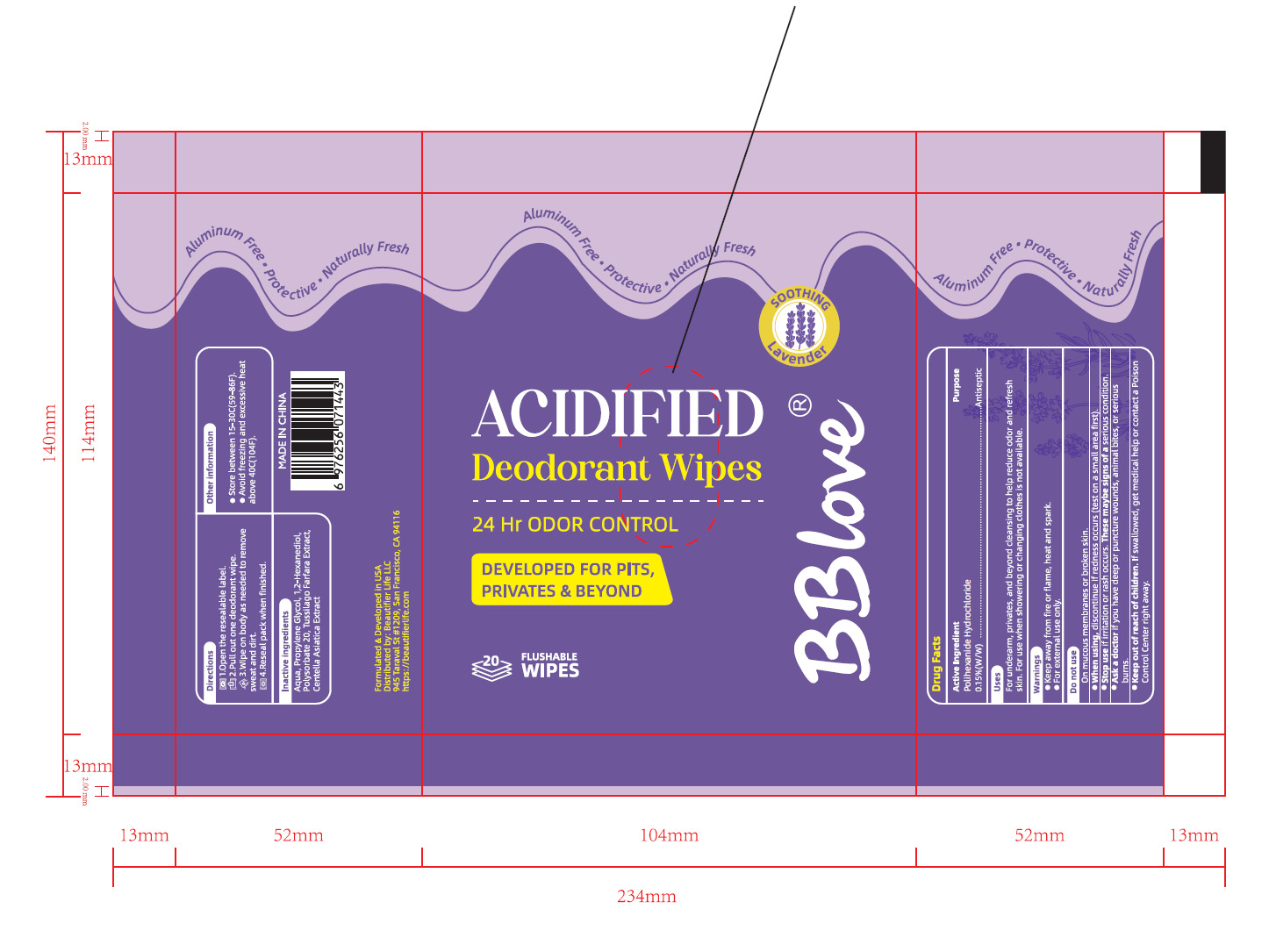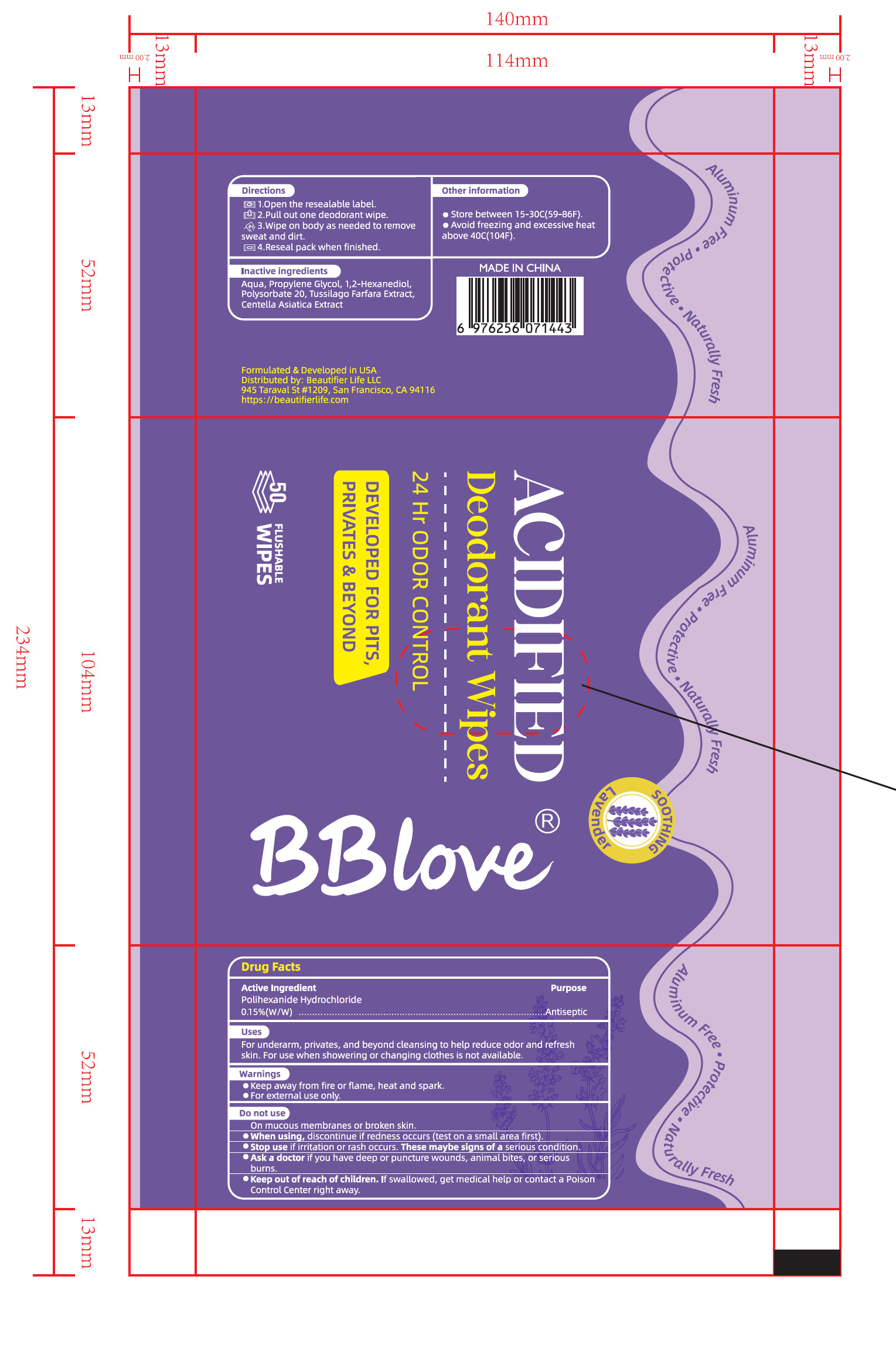 DRUG LABEL: BBlove Acidified Deodorant Wipes
NDC: 43116-046 | Form: CLOTH
Manufacturer: Shenzhen Shierjie Biological Engineering Co., LTD
Category: otc | Type: HUMAN OTC DRUG LABEL
Date: 20250921

ACTIVE INGREDIENTS: POLIHEXANIDE HYDROCHLORIDE 0.15 U/100 U
INACTIVE INGREDIENTS: AQUA; PROPYLENE GLYCOL; 1,2-HEXANEDIOL; POLYSORBATE 20; TUSSILAGO FARFARA; CENTELLA ASIATICA TRITERPENOIDS

43116-046

Active Ingredient

Polihexanide Hydrochloride 0.1 5%(W/W)

Purpose

Antiseptic

Use

For underarm, privates, and beyond cleansing to help reduce odor and rfesh
skin. For use when showering or changing clothes is not available.

Warnings

●Keep away from fire or flame, heat and spark.
●For external use only.

Do not use

On mucous membranes or broken skin.

When Using

●When using, discontinue if redness occurs (test on a small area first).

Stop Use

Stop use amitation or rash oC Thee maybe signs ofa serious condion

Keep Oot Of Reach Of Children

Keep out of reach of children. nn swallol Control Center right away.Swa lowed, get medical help or contact a Poison

Directions

1.Open the resealable label.
2.Pull out one deodorant wipe.
3.Wipe on body as needed to remove sweat and dirt.
4.Reseal pack when finished.

Other information

●Store between 15-30C(59-86F).
●Avoid freezing and excessive heat above 40C(104F).

Inactive ingredients

Aqua, Propylene Glycol, 1,2-Hexanediol,
Polysorbate 20, Tussilago Farfara Extract,
Centella Asiatica Extract